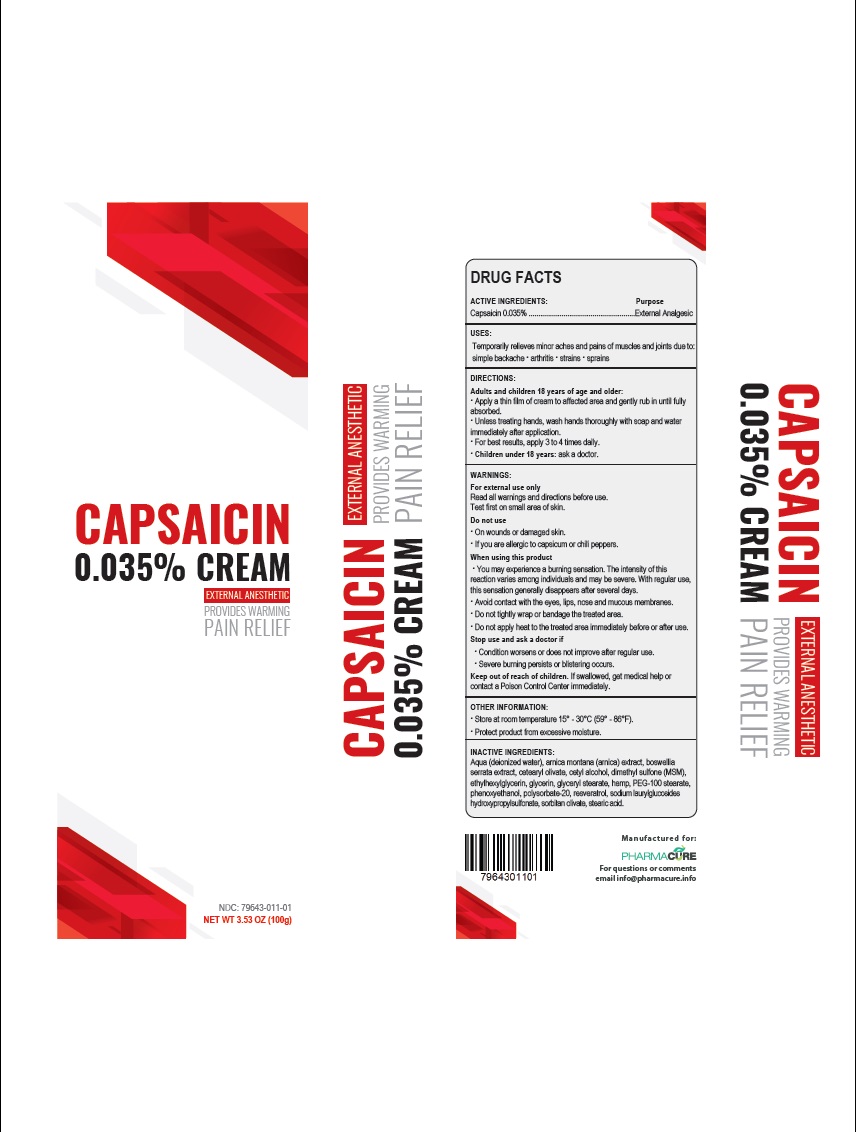 DRUG LABEL: Capsaicin
NDC: 79643-011 | Form: CREAM
Manufacturer: PHARMACURE LLC
Category: otc | Type: HUMAN OTC DRUG LABEL
Date: 20250204

ACTIVE INGREDIENTS: CAPSAICIN 0.035 g/100 g
INACTIVE INGREDIENTS: WATER; ARNICA MONTANA FLOWER; BOSWELLIA SERRATA WHOLE; CETEARYL OLIVATE; CETYL ALCOHOL; DIMETHYL SULFONE; ETHYLHEXYLGLYCERIN; GLYCERIN; GLYCERYL MONOSTEARATE; HEMP; PEG-100 MONOSTEARATE; PHENOXYETHANOL; POLYSORBATE 20; RESVERATROL; SODIUM LAURYLGLUCOSIDES HYDROXYPROPYLSULFONATE; SORBITAN OLIVATE; STEARIC ACID

Active Ingredient Purpose

Capsaicin 0.035% External Analgesic

Uses

Temporarily relieves minor aches and pains of muscles and joints due to:

- simple backache
- arthritis
- strains,
- sprains

Warnings

For external use only

Read all warnings and directions before use.

Test first on small area of skin.

Do not use

• On wounds or damaged skin.

• If you are allergic to capsicum or chili peppers.

When using this product

• You may experience a burning sensation. The intensity of this reaction varies among individuals and may be severe. With regular use, this sensation generally disappears after several days.

• Avoid contact with the eyes, lips, nose and mucous membranes

• Do not tightly wrap or bandage the treated area

• Do not apply heat to the treated area immediately before or after use.

Stop use and ask a doctor if

• Conditions worsens or does not improve after regular use.
• Severe burning persists o blistering occurs.

Keep out of reach of children. If swallowed, get medical help or contact a Poison Control Center immediately.

Directions

Adults and children 18 years of age and older:

- Apply a thin film of cream to affected area and gently rub in until fully absorbed.
- Unless treating hands, wash hands thoroughly with soap and water immediately after application.
- For best results, apply 3 to 4 times daily.
- Children under 18 years: ask a doctor

Other Information

- Store at room temperature 15°-30°C (59°-86°F).
- Protect product from excessive moisture.

Inactive ingredients

Aqua (deionized water), arnica montana (arnica) extract, boswellia serrata extract, cetearyl olivate, cetyl alcohol, dimethyl sulfone (MSM), ethylhexylglycerin, glycerin, glyceryl stearate, hemp, sodium laurylglucosides hydroxypropylsulfonate, PEG-100 stearate, phenoxyethanol, polysorbate-20, resveratrol, sodium laurylglucosides hydroxypropylsulfonate, sorbitan olivate, stearic acid